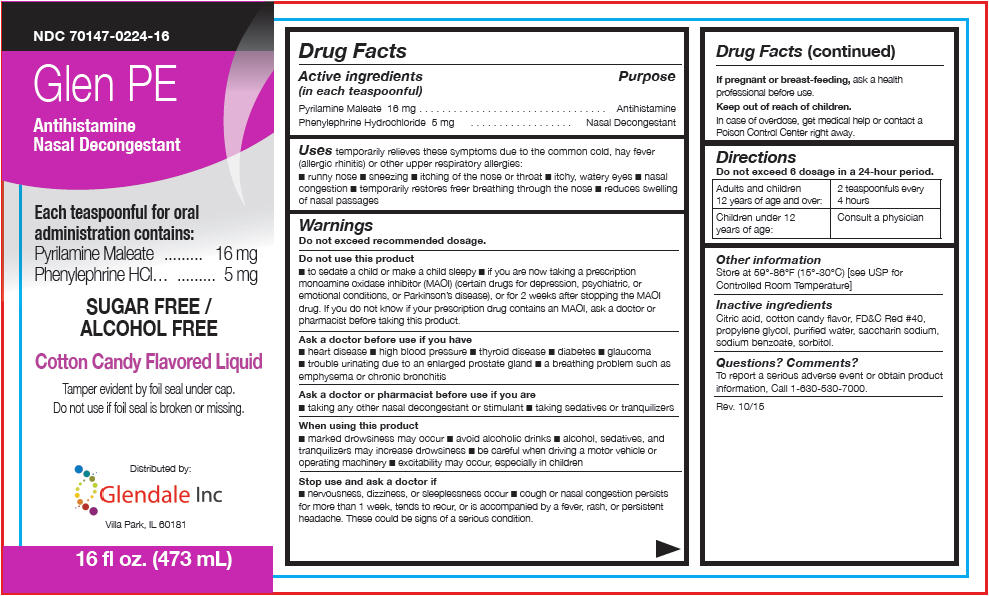 DRUG LABEL: Glen PE
NDC: 70147-224 | Form: SYRUP
Manufacturer: Glendale Inc
Category: otc | Type: HUMAN OTC DRUG LABEL
Date: 20151209

ACTIVE INGREDIENTS: PHENYLEPHRINE HYDROCHLORIDE 15 mg/5 mL; PYRILAMINE MALEATE 16 mg/5 mL
INACTIVE INGREDIENTS: CITRIC ACID MONOHYDRATE; PROPYLENE GLYCOL; WATER; SACCHARIN SODIUM; SODIUM BENZOATE; SORBITOL; FD&C red no. 40

Glen PE

Drug Facts

ACTIVE INGREDIENT

Active ingredients (in each teaspoonful) | Purpose
Pyrilamine Maleate 16 mg | Antihistamine
Phenylephrine Hydrochloride 5 mg | Nasal Decongestant

Uses

temporarily relieves these symptoms due to the common cold, hay fever (allergic rhinitis) or other upper respiratory allergies:

- runny nose
- sneezing
- itching of the nose or throat
- itchy, watery eyes
- nasal congestion
- temporarily restores freer breathing through the nose
- reduces swelling of nasal passages

Warnings

Do not exceed recommended dosage.

Do not use this product

- to sedate a child or make a child sleepy
- if you are now taking a prescription monoamine oxidase inhibitor (MAOI) (certain drugs for depression, psychiatric, or emotional conditions, or Parkinson's disease), or for 2 weeks after stopping the MAOI drug. If you do not know if your prescription drug contains an MAOI, ask a doctor or pharmacist before taking this product.

Ask a doctor before use if you have

- heart disease
- high blood pressure
- thyroid disease
- diabetes
- glaucoma
- trouble urinating due to an enlarged prostate gland
- a breathing problem such as emphysema or chronic bronchitis

Ask a doctor or pharmacist before use if you are

- taking any other nasal decongestant or stimulant
- taking sedatives or tranquilizers

When using this product

- marked drowsiness may occur
- avoid alcoholic drinks
- alcohol, sedatives, and tranquilizers may increase drowsiness
- be careful when driving a motor vehicle or operating machinery
- excitability may occur, especially in children

Stop use and ask a doctor if

- nervousness, dizziness, or sleeplessness occur
- cough or nasal congestion persists for more than 1 week, tends to recur, or is accompanied by a fever, rash, or persistent headache. These could be signs of a serious condition.

PREGNANCY OR BREAST FEEDING

If pregnant or breast-feeding, ask a health professional before use.

Keep out of reach of children.

In case of overdose, get medical help or contact a Poison Control Center right away.

Directions

Do not exceed 6 dosage in a 24-hour period.

Adults and children 12 years of age and over: | 2 teaspoonfuls every 4 hours
Children under 12 years of age: | Consult a physician

Other information

Store at 59°-86°F (15°-30°C) [see USP for Controlled Room Temperature]

Inactive ingredients

Citric acid, cotton candy flavor, FD&C Red #40, propylene glycol, purified water, saccharin sodium, sodium benzoate, sorbitol.

Questions? Comments?

To report a serious adverse event or obtain product information, Call 1-630-530-7000.

Distributed by:
Glendale Inc
Villa Park, IL 60181

PRINCIPAL DISPLAY PANEL - 473 mL Bottle Label

NDC 70147-0224-16

Glen PE

Antihistamine
Nasal Decongestant

Each teaspoonful for oral
administration contains:
Pyrilamine Maleate 16 mg
Phenylephrine HCl 5 mg

SUGAR FREE /
ALCOHOL FREE

Cotton Candy Flavored Liquid

Tamper evident by foil seal under cap.
Do not use if foil seal is broken or missing.

Distributed by:
Glendale Inc
Villa Park, IL 60181

16 fl oz. (473 mL)